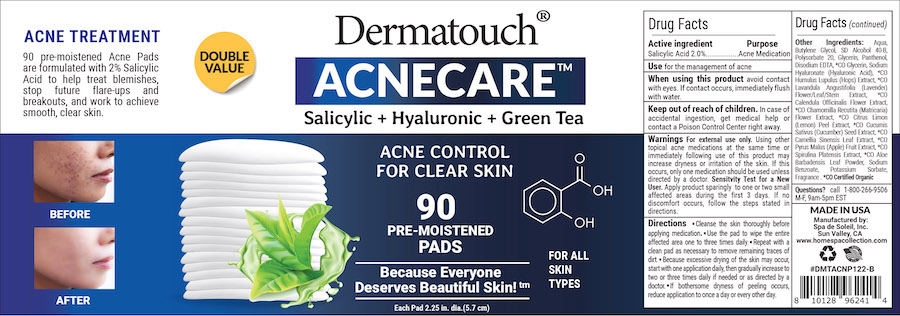 DRUG LABEL: Dermatouch Acnecare Pads
NDC: 68062-2256 | Form: LIQUID
Manufacturer: Spa de Soleil
Category: otc | Type: HUMAN OTC DRUG LABEL
Date: 20260121

ACTIVE INGREDIENTS: SALICYLIC ACID 1 mg/100 mL
INACTIVE INGREDIENTS: BUTYLENE GLYCOL; POLYSORBATE 20; GLYCERIN; PANTHENOL; HYALURONIC ACID; WATER

Dermatouch Acnecare Pads

Active ingredient Purpose

Salicylic Acid (2.0%)..........Acne Treatment

Purpose

Acne Treatment

INDICATIONS AND USAGE

For treatment of acne

Warnings

For external use only. Using other topical acne medications at the same time or immediately following use of this product may increase dryness or irritation of the skin. If this occurs, only one medication should be used unless directed by a doctor. Sensitivity Test for a New User. Apply product sparingly to one or two small, affected areas during the first 3 days. If no discomfort occurs, follow the steps stated in directions.

Keep out of reach of children. In case of accidental ingestion, get medical help or contact a Poison Control Center right away.

When using this product

• Skin irritation and dryness is more likely to occur if you use another topical acne medication while using this product. If irritation occurs, use only one topical acne medication at a time.

Directions

Cleanse the skin thoroughly before applying medication. Use the pad to wipe the entire affected area one to three times daily. Repeat with a clean pad as necessary to remove remaining traces of dirt. Because excessive drying of the skin may occur, start with one application daily, then gradually increase to two or three times daily if needed or as directed by a doctor. If bothersome dryness of peeling occurs, reduce application to once a day or every other day.

INACTIVE INGREDIENT

Other Ingredients:

Aqua, Butylene Glycol, SD Alcohol 40-B, Polysorbate 20, Glycerin, Panthenol, Disodium EDTA, *CO Glycerin, Sodium Hyaluronate (Hyaluronic Acid), *CO Humulus Lupulus (Hops) Extract, *CO Lavandula Angustifolia (Lavender) Flower/Leaf/Stem Extract, *CO Calendula Officinalis Flower Extract, *CO Chamomilla Recutita (Matricaria) Flower Extract, *CO Citrus Limon (Lemon) Peel Extract, *CO Cucumis Sativus (Cucumber) Seed Extract, *CO Camellia Sinensis Leaf Extract, *CO Pyrus Malus (Apple) Fruit Extract, *CO Spirulina Platensis Extract, *CO Aloe Barbadensis Leaf Powder, Sodium Benzoate, Potassium Sorbate, Fragrance . *CO Certified Organic